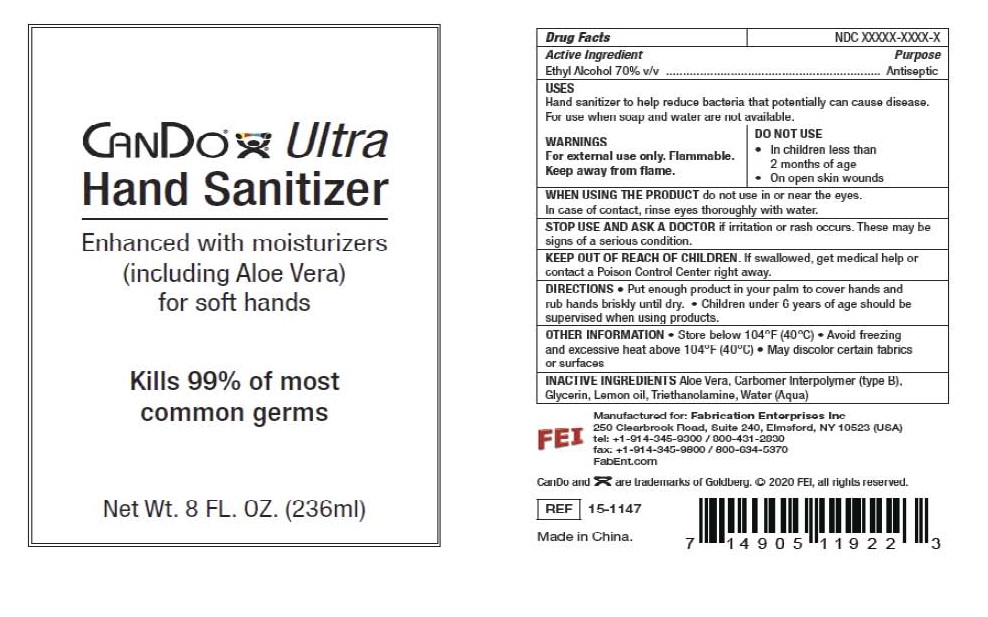 DRUG LABEL: CANDO Ultra Hand Sanitizer
NDC: 51452-108 | Form: GEL
Manufacturer: Fabrication Enterprises
Category: otc | Type: HUMAN OTC DRUG LABEL
Date: 20200928

ACTIVE INGREDIENTS: ALCOHOL 70 mL/100 mL
INACTIVE INGREDIENTS: TROLAMINE; GLYCERIN; WATER; ALOE VERA LEAF; CARBOMER INTERPOLYMER TYPE B (ALLYL PENTAERYTHRITOL CROSSLINKED); LEMON OIL

CANDO Ultra
Hand Sanitizer

Active Ingredient

Ethyl Alcohol 70% v/v

Purpose

Antiseptic

USES

Hand sanitizer to help reduce bacteria that potentially can cause disease. For use when soap and water are not available.

WARNINGS

For external use only. Flammable.

Keep away from flame.

DO NOT USE

- In children less than 2 months of age
- On open skin wounds

WHEN USING

WHEN USING THE PRODUCT do not use in or near the eyes. In case of contact, rinse eyes thoroughly with water.

STOP USE AND ASK A DOCTOR if irritation or rash occurs.

These may be signs of a serious condition.

KEEP OUT OF REACH OF CHILDREN. If swallowed, get medical help or contact a Poison Control Center right away.

DIRECTIONS

●Put enough product in your palm to cover hands and rub hands briskly until dry.

●Children under 6 years of age should be supervised when using products.

OTHER INFORMATION

●Store below 104°F (40°C)

●Avoid freezing and excessive heat above 104°F (40°C)

●May discolor certain fabrics or surfaces

INACTIVE INGREDIENTS

Aloe Vera, Carbomer Interpolymer (type B), Glycerin, Lemon oil, Triethanolamine, Water (Aqua)